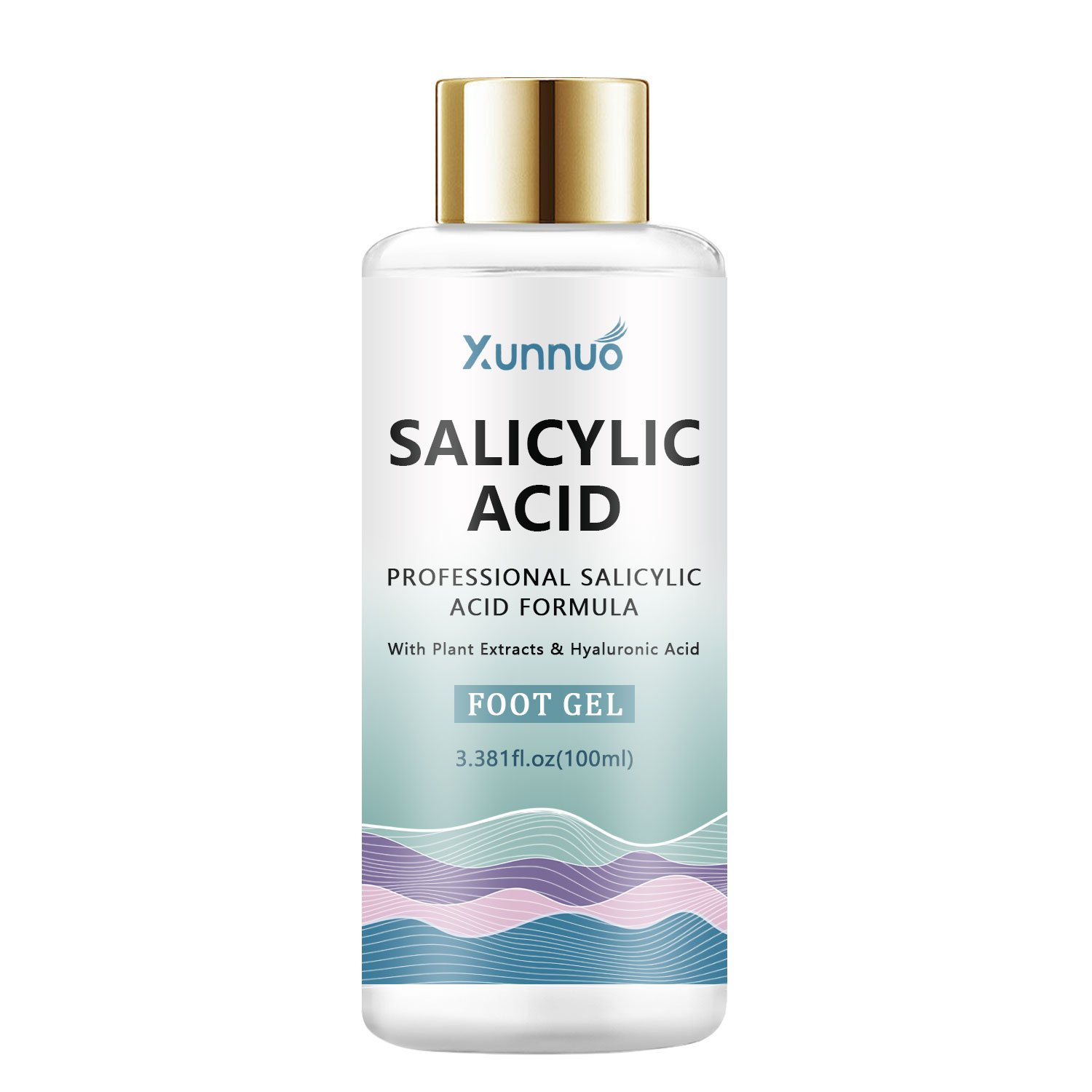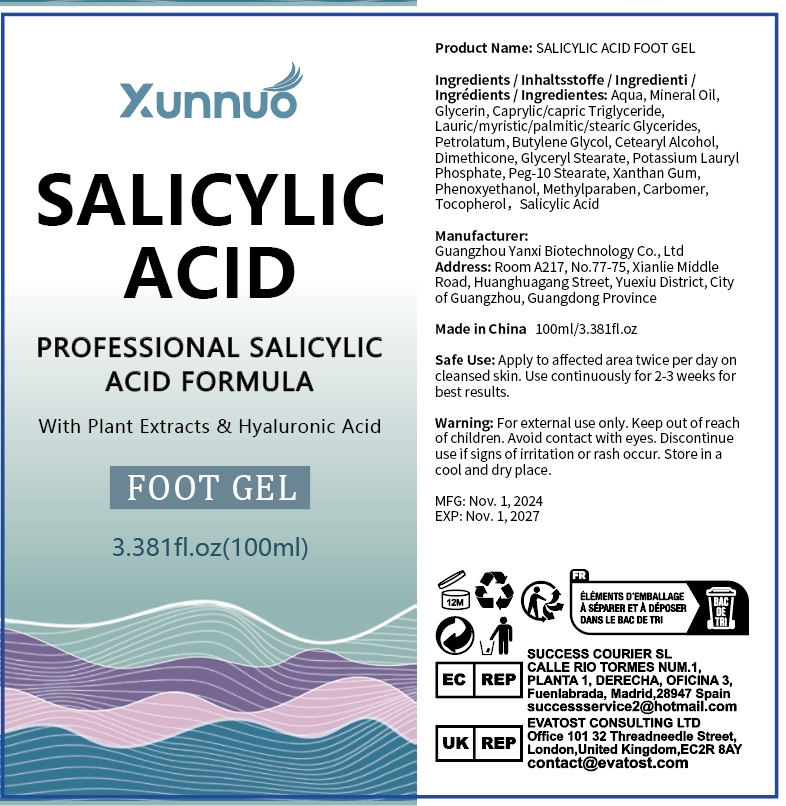 DRUG LABEL: Salicylic Acid Foot Gel
NDC: 84025-260 | Form: GEL
Manufacturer: Guangzhou Yanxi Biotechnology Co., Ltd
Category: otc | Type: HUMAN OTC DRUG LABEL
Date: 20241113

ACTIVE INGREDIENTS: MINERAL OIL 5 mg/100 mL; GLYCERIN 3 mg/100 mL
INACTIVE INGREDIENTS: WATER

DOSAGE AND ADMINISTRATION

Apply to affected area twice per day on
cleansed skin.Use continuously for 2-3 weeks for
Dest results.

WARNINGS

Keep out of children

INACTIVE INGREDIENT

Aqua

INDICATIONS AND USAGE

for daily foot care

keep out of children

PURPOSE

Foot exfoliation and hydration